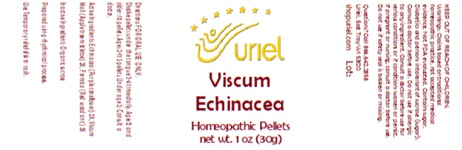 DRUG LABEL: Viscum Echinacea
NDC: 48951-9075 | Form: PELLET
Manufacturer: Uriel Pharmacy Inc.
Category: homeopathic | Type: HUMAN OTC DRUG LABEL
Date: 20251208

ACTIVE INGREDIENTS: ECHINACEA, UNSPECIFIED 2 [hp_X]/1 1; VISCUM ALBUM FRUITING TOP 2 [hp_X]/1 1; FORMICA RUFA 3 [hp_X]/1 1
INACTIVE INGREDIENTS: SUCROSE

Viscum Echinacea

INDICATIONS AND USAGE

Directions: FOR ORAL USE ONLY.

DOSAGE AND ADMINISTRATION

Dissolve pellets under the tongue 3-4 times daily. Ages 12 and older: 10 pellets. Ages 2-11: 5 pellets. Under age 2: Consult a doctor.

ACTIVE INGREDIENT

Active Ingredients: Echinacea (Purple coneflower) 2X, Viscum Mali (Apple tree mistletoe) 2X, Formica (Red wood ant) 3X

Inactive Ingredient: Organic sucrose

Prepared using rhythmical processes.

PURPOSE

Use: Temporary relief of skin rash.

KEEP OUT OF REACH OF CHILDREN.

WARNINGS

Warnings: Claims based on traditional homeopathic practice, not accepted medical evidence. Not FDA evaluated. Contains sugar. Diabetics and persons intolerant of sucrose (sugar): Consult a doctor before use. Do not use if allergic to any ingredient Consult a doctor before use for serious conditions or if conditions worsen or persist. If pregnant or nursing, consult a doctor before use. Do not use if safety seal is broken or missing.

Questions? Call 866.642.2858
Uriel, East Troy WI 53120
shopuriel.com Lot: